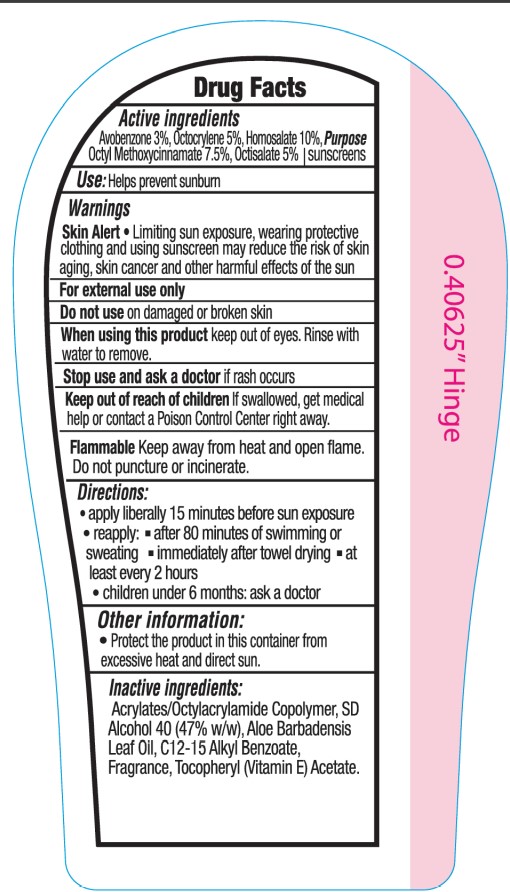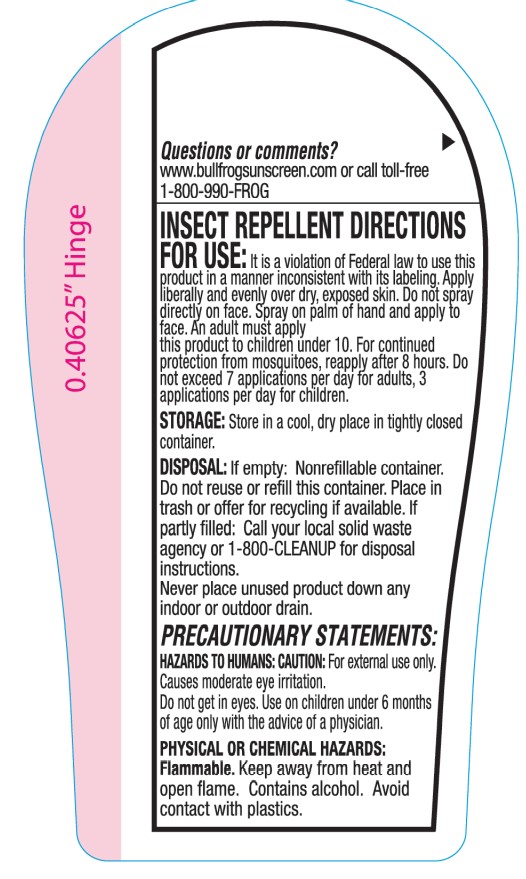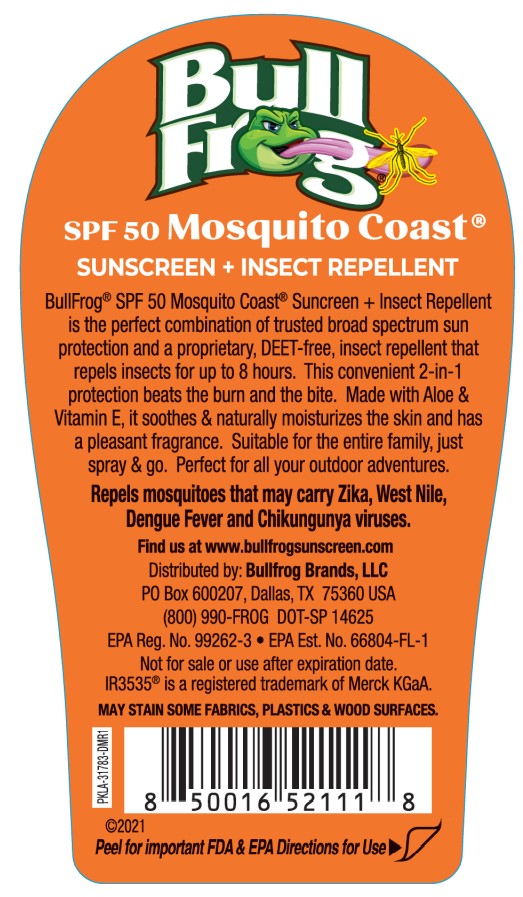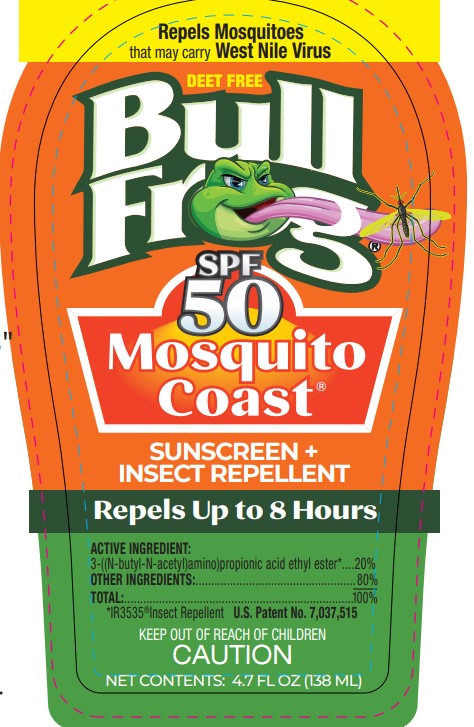 DRUG LABEL: Bullfrog
NDC: 58443-0517 | Form: SPRAY
Manufacturer: Prime Enterprises Inc.
Category: otc | Type: HUMAN OTC DRUG LABEL
Date: 20220117

ACTIVE INGREDIENTS: OCTISALATE 44.25 mg/1 mL; OCTINOXATE 66.38 mg/1 mL; AVOBENZONE 26.55 mg/1 mL; OCTOCRYLENE 44.25 mg/1 mL; HOMOSALATE 88.5 mg/1 mL
INACTIVE INGREDIENTS: ALKYL (C12-15) BENZOATE; ETHYL BUTYLACETYLAMINOPROPIONATE; ALCOHOL; ALOE VERA LEAF; .ALPHA.-TOCOPHEROL ACETATE; WATER

Bullfrog SPF 50 Moquito Coast Sunscreen + Insect Repellent

Active Ingredients

Avobenzone 3%

Homosalate 10%

Octisalate 5%

Octocrylene 5%

Octinoxate 7.5%

Purpose

Sunscreens

Uses

Helps prevent sunburn

Warnings

Skin Alert

- Limiting sun exposure, wearing protective clothing and using sunscreen may reduce the risk of skin aging, skin care and other harmful effects of the sun

WARNINGS

For external use only

Do not use on damaged or broken skin

When using this product keep out of eyes. Rinse with water to remove.

Stop use and ask a doctor if rash occurs

Keep out of reach of children. If swallowed, get medical help or contact a Poison Control Center right away.

Flammable Keep away from heat and open flame. Do not puncture or incinerate.

Directions

- apply liberally 15 minutes before sun exposure
- reapply:
- after 80 minutes of swimming or sweating
- immediately after towel drying
- at least every 2 hours
- children under 6 months: Ask a doctor

Other Information

- protect the product in this container from excessive heat and direct sun.

INACTIVE INGREDIENT

Acrylates/Octylacrylamide Copolymer, Aloe Barbadensis Leaf Juice, Butyl Methoxydibenzoylmethane, C12-15 Alkyl Benzoate, Ethyl Butylacetylaminopropionate, Ethylhexyl Salicylate, Homosalate, Octinoxate (Ethylhexyl Methoxycinnamate), Octocrylene, SD Alcohol 40 (Alcohol Denat.), Tocopheryl Acetate, Water

Question or comments?

www.bullfrogsunscreen.com or call toll-free

1-800-990-FROG